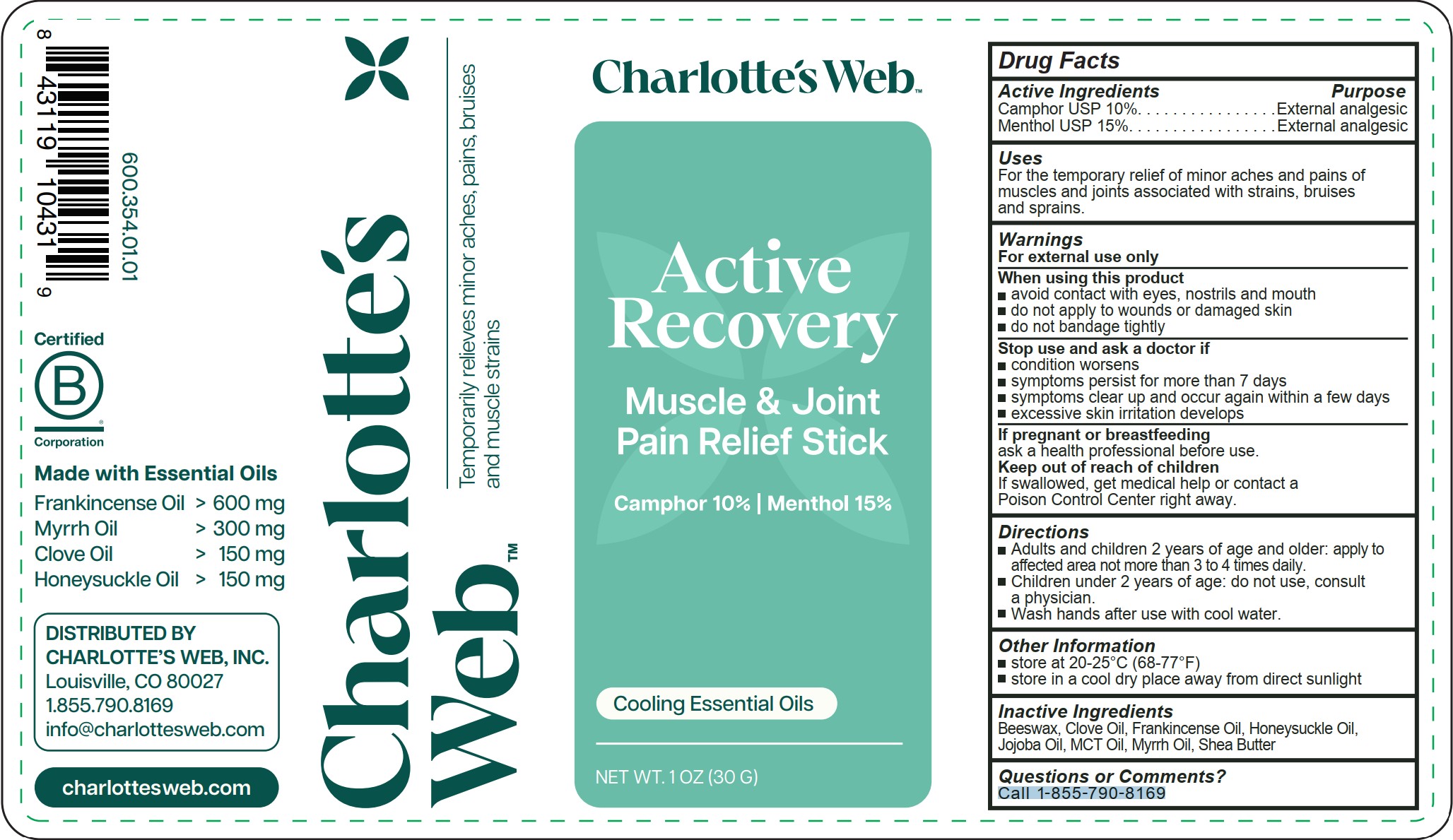 DRUG LABEL: Active Recovery Pain Relief Stick
NDC: 79845-769 | Form: STICK
Manufacturer: Charlotte’s Web, Inc.
Category: otc | Type: HUMAN OTC DRUG LABEL
Date: 20250801

ACTIVE INGREDIENTS: CAMPHOR (NATURAL) 10 g/100 g; MENTHOL 15 g/100 g
INACTIVE INGREDIENTS: FRANKINCENSE OIL; LONICERA CAPRIFOLIUM FLOWER; BEESWAX; CLOVE OIL; MYRRH OIL; MEDIUM-CHAIN TRIGLYCERIDES; SHEA BUTTER; JOJOBA OIL

Active Recovery Pain Relief Stick

Active ingredients

Camphor USP 10%

Menthol USP 15%

Purpose

Camphor USP 10%.......................External analgesic

Menthol USP 15%.........................External analgesic

Uses

For the temporary relief of minor aches and pains of muscles and joints associated with strains, bruises and sprains.

Warnings

For external use only

When using this product

- avoid contact with eyes, nostrils and mouth
- do not apply to wounds or damaged skin
- do not bandage tightly

Stop use and ask a doctor if

- condition worsens
- symptoms persist for more than 7 days
- symptoms clear up and occur again within a few days
- excessive skin irritation develops

PREGNANCY OR BREAST FEEDING

If pregnant or breastfeeding, ask a health professional before use.

Keep out of reach of children. If swallowed, get medical help or contact a Poison Control Center right away

Directions

- Adults and children 2 years of age and older: apply to affected area not more than 3 to 4 times daily.
- Children under 2 years of age: do not use, consult a physician.
- Wash hands after use with cool water

Other information

- store at 20-25°C (68-77°F)
- store in a cool dry place away from direct sunlight

Inactive ingredients

Beeswax, Clove Oil, Frankincense Oil, Honeysuckle Oil, Jojoba Oil, MCT Oil, Myrrh Oil, Shea Butter

Questions or Comments?

Call 1-855-790-8169

PACKAGE LABEL

Charlotte's Web

Active Recovery

Muscle & Joint Pain Relief Stick

Camphor 10% | Menthol 15%

Cooling Essential Oils

NET WT. 1 OZ (30 G)